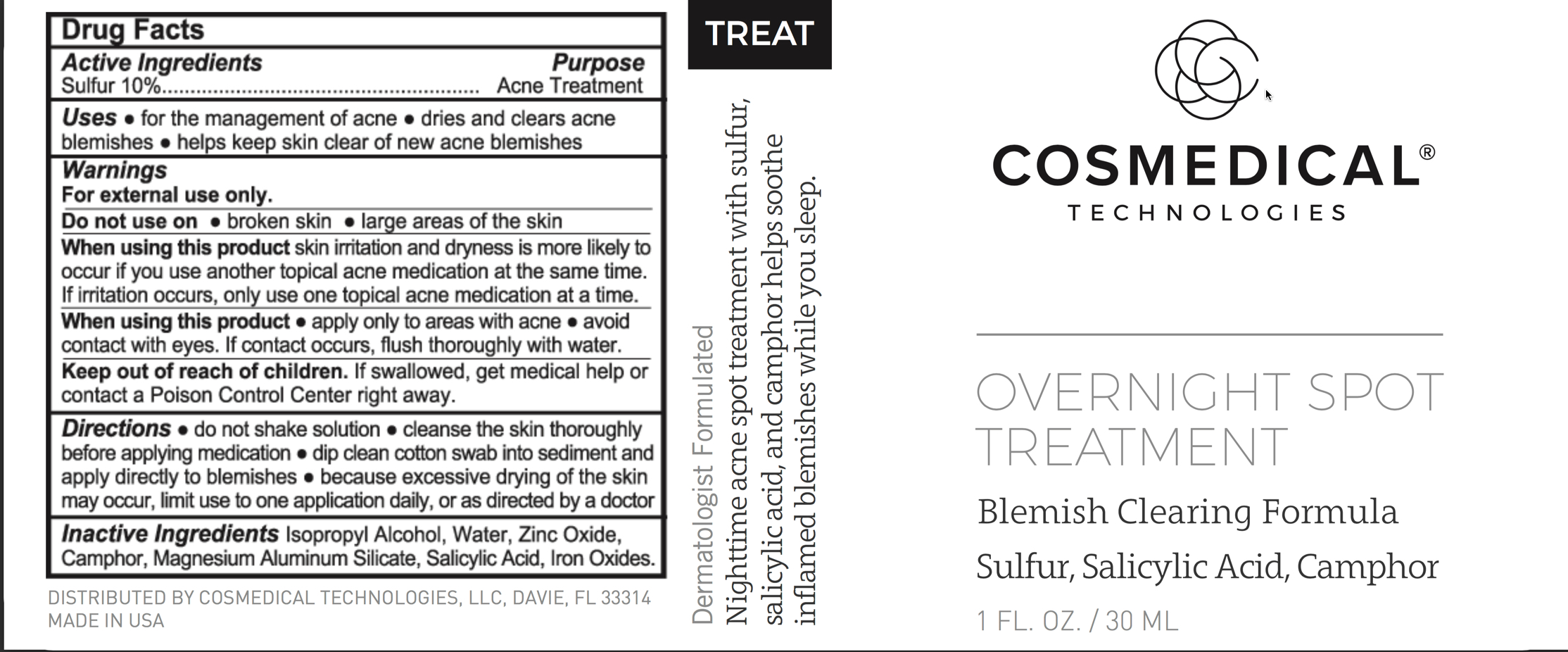 DRUG LABEL: Overnight Spot Treatment
NDC: 70060-1506 | Form: LIQUID
Manufacturer: CosMedical Technologies
Category: otc | Type: HUMAN OTC DRUG LABEL
Date: 20251113

ACTIVE INGREDIENTS: SULFUR 100 mg/1 mL
INACTIVE INGREDIENTS: ISOPROPYL ALCOHOL; ZINC OXIDE; WATER

Overnight Spot Treatment

PURPOSE

Acne Treatment

WARNINGS

For external use only

Keep out of reach of children.

INACTIVE INGREDIENT

Isopropyl Alcohol, Water, Zinc Oxide, Camphor, Magnesium Aluminum Silicate, Salicylic Acid, Iron Oxides.

ACTIVE INGREDIENT

Sulfur 10%

DOSAGE AND ADMINISTRATION

Topical

INDICATIONS AND USAGE

Acne Treatment